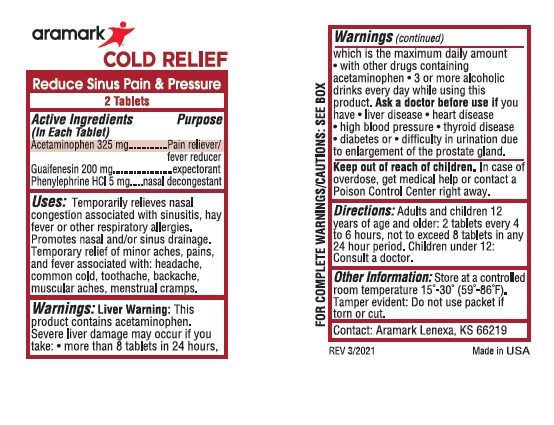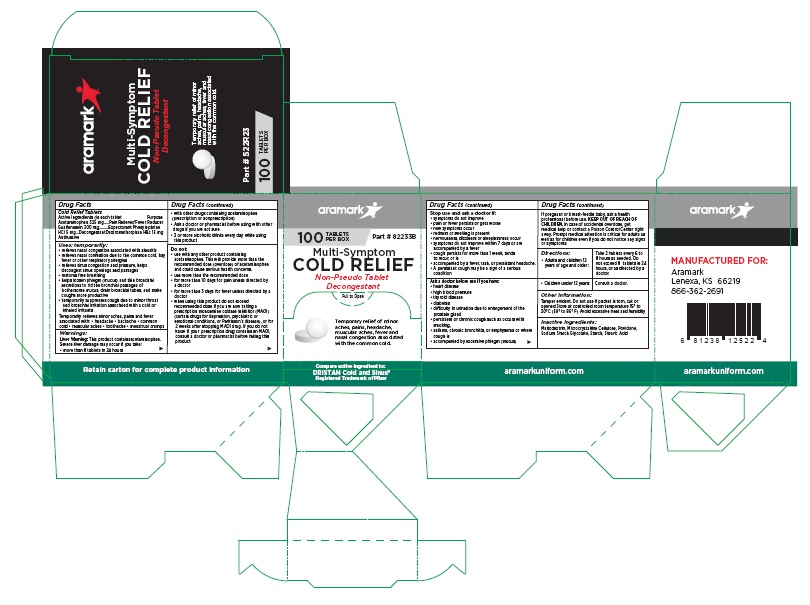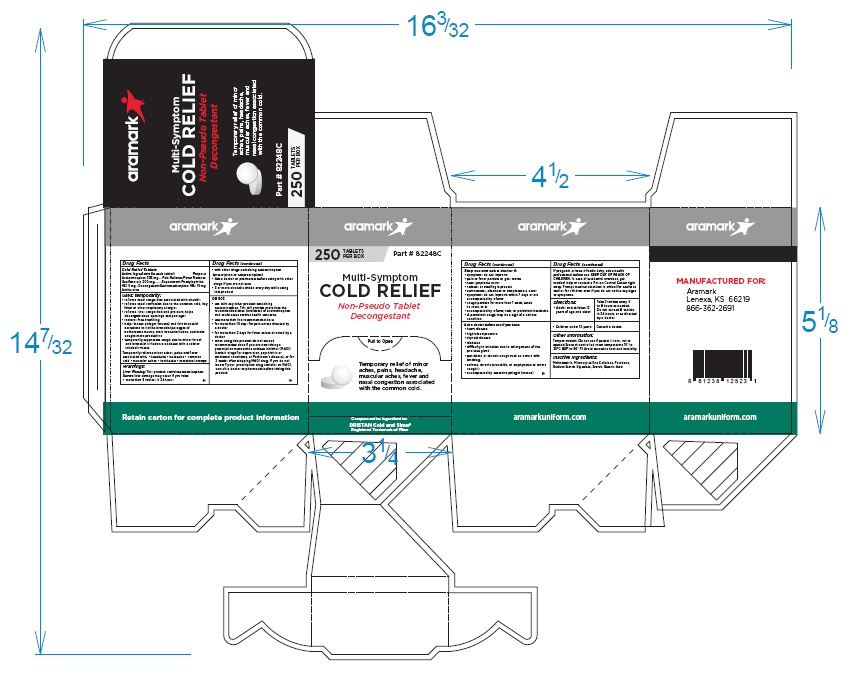 DRUG LABEL: Aramark Multi-Symptom Cold Relief
NDC: 81238-0107 | Form: TABLET
Manufacturer: Western First Aid Safety DBA Aramark
Category: otc | Type: HUMAN OTC DRUG LABEL
Date: 20210603

ACTIVE INGREDIENTS: ACETAMINOPHEN 325 mg/1 1; GUAIFENESIN 200 mg/1 1; PHENYLEPHRINE HYDROCHLORIDE 5 mg/1 1; DEXTROMETHORPHAN HYDROBROMIDE 15 mg/1 1
INACTIVE INGREDIENTS: MALTODEXTRIN; CELLULOSE, MICROCRYSTALLINE; POVIDONE; SODIUM STARCH GLYCOLATE TYPE A CORN; STARCH, CORN; STEARIC ACID

Aramark Multi-Symptom Cold Relief

Drug Facts

Cold Relief Tablets
Active Ingredients (in each tablet)
Acetaminophen 325 mg
Guaifenesein 200 mg
Phenylephrine HCl 5 mg
Dextromethorphan HBr 15 mg

Purpose
Acetaminophen.....................Pain Reliever/Fever Reducer
Guaifenesein ........................Expectorant
Phenylephrine HCl ...............Decongestant
Dextromethorphan HBr. .......Antitussive

INDICATIONS AND USAGE

Uses: temporarily:
• relieves nasal congestion associated with sinusitis
• relieves nasal confestion due to the common cold, hay
fever or other respiratory allergies
• relieves sinus congestion and pressure, helps
decongest sinus openings and passages
• restores free breathing
• helps loosen phlegm (mucus) and thin bronchial
secretions to rid the bronchial passages of
bothersome mucus, drain bronchial tubes, and make
coughs more productive
• temporarily suppresses cough due to minor throat
and bronchial irritation associated with a cold or
inhaled irritants
Temporarily relieves minor aches, pains and fever
associated with: • headache • backache • common
cold • muscular aches • toothache • menstrual cramps
o make coughs more productive

Warnings:
Liver Warning: This product containsacetaminophen.
Severe liver damage may occur if you take:
• more than 8 tablets in 24 hours
• with other drugs containing acetaminophen
(prescription or nonprescription)
• Ask a doctor or pharmacist before using with other
drugs if you are not sure
• 3 or more alcoholic drinks every day while using
this product.

Do not:
• use with any other product containing
acetaminophen. This will provide more than the
recommended dose (overdose) of acetaminophen
and could cause serious health concerns.
• use more than the recommended dose
• for more than 10 days for pain unless directed by
a doctor
• for more than 3 days for fever unless directed by a
doctor
• when using this product do not exceed
recommended dose if you are now taking a
prescription monoamine oxidase inhibitor (MAOI)
(certain drugs for depression, psychiatric or
emotional conditions, or Parkinson’s disease), or for
2 weeks after stopping MAOI drug. If you do not
know if your prescription drug contains an MAOI,
consult a doctor or pharmacist before taking this
product

Stop use and ask a doctor if:

• symptoms do not improve
• pain or fever persists or gets worse
• new symptoms occur
• redness or swelling is present
• nervousness, dizziness or sleeplessness occur
• symptoms do not improve within 7 days or are
accompanied by a fever
• cough persists for more than 1 week, tends
to recur, or is
• accompanied by a fever, rash, or persistant headache.
• A persistant cough may be a sign of a serious
condition

Ask a doctor before use if you have:
• heart disease
• high blood pressure
• thyroid disease
• diabetes
• difficulty in urination due to enlargement of the
prostate gland
• persistent or chronic cough such as occurs with
smoking,
• asthma, chronic bronchitis, or emphysema or where
cough is
• accompanied by excessive phlegm (mucus)

PREGNANCY

If pregnant or breast-feedin baby, ask a health
professional before use.

KEEP OUT OF REACH OF CHILDREN. In case of accidental overdose, get
medical help or contact a Poison Control Center right
away. Prompt medical attention is critical for adults as
well as for children even if you do not notice any signs
or symptoms.

Directions:
• Adults and children 12 years of age and older: | Take 2 tablets every 6 to 8 hours as needed. Do not exceed 8 tablets in 24 hours, or as directed by a doctor.
• Children under 12 years: | Consult a doctor.

Other Information:
Tamper evident. Do not use if packet is torn, cut or
opened Store at controlled room temperature 15° to
30°C (59° to 86° F) Avoid excessive heat and humidity

Inactive Ingredients:
Maltodextrin, Microcrystalline Cellulose, Povidone,
Sodium Starch Glycolate, Starch, Stearic Acid

Product Labeling

aramark

100 TABLETS
PER BOX Part # 82233B

Multi-Symptom
COLD RELIEF

Non-Pseudo Tablet
Decongestant

Temporary relief of minor
aches, pains, headache,
muscular aches, fever and
nasal congestion associated
with the common cold.

Compare active ingredient to:
DRISTAN Cold and Sinus®
Registered Trademark of Pfizer

Retain carton for complete product information

MANUFACTURED FOR:

Aramark
Lenexa, KS 66219
866-362-2691

aramarkuniform.com

100 Tablet Box

250 Tablet Box

2-Tablet Packet

res